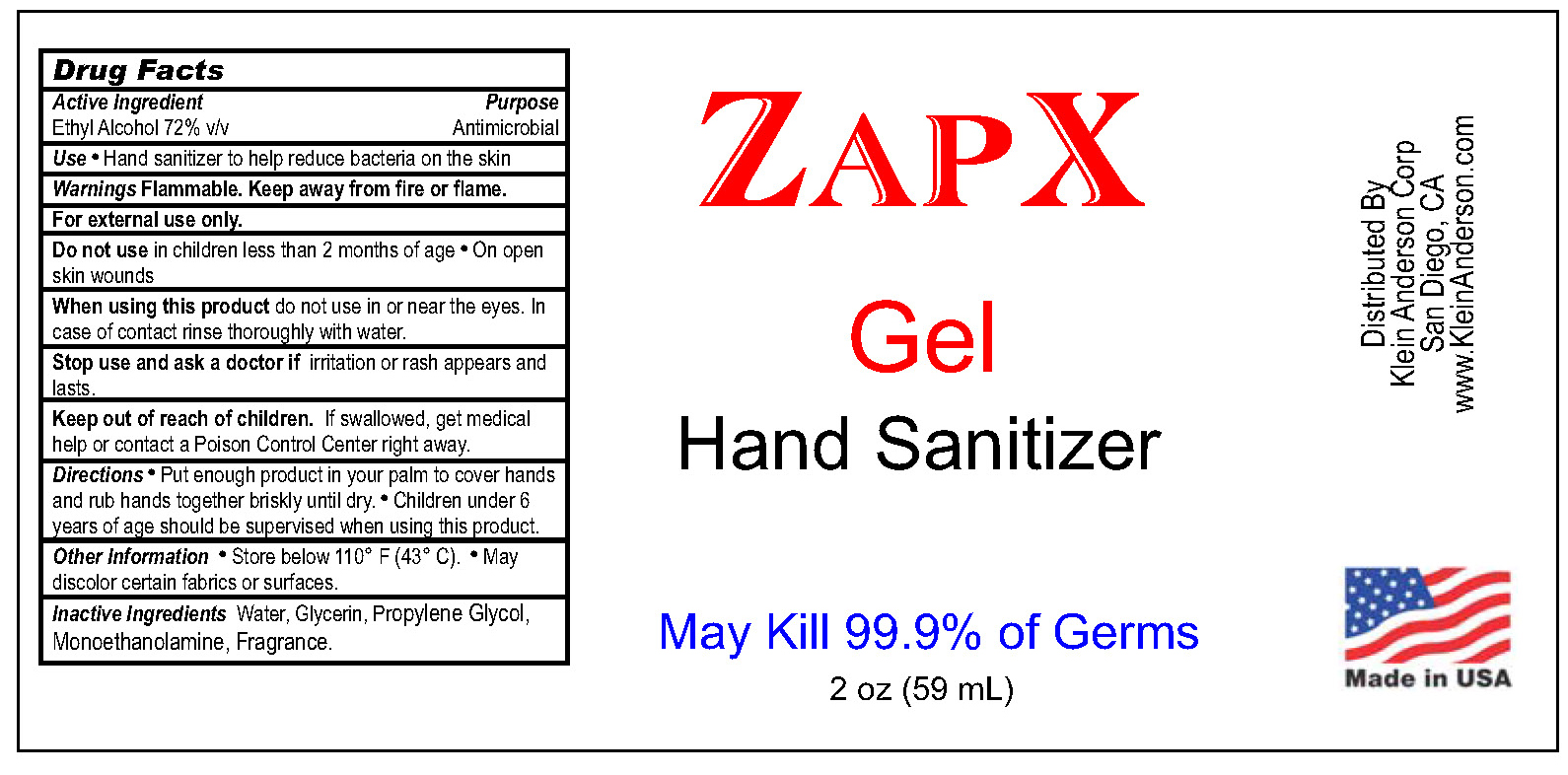 DRUG LABEL: KAC Zapx Hand Sanitizer
NDC: 78919-102 | Form: GEL
Manufacturer: Klein Anderson Corp
Category: otc | Type: HUMAN OTC DRUG LABEL
Date: 20200610

ACTIVE INGREDIENTS: ALCOHOL 72 mL/100 mL
INACTIVE INGREDIENTS: MONOETHANOLAMINE 1 mL/100 mL; PROPYLENE GLYCOL 1 mL/100 mL; GLYCERIN 1 mL/100 mL; WATER 1 mL/100 mL

Hand Sanitizer

Active Ingredient(s)

Ethyl Alcohol 72% v/v. Purpose: Antimicrobial

Purpose

Antimicrobial, Hand Sanitizer

Use

Hand Sanitizer to help reduce bacteria that potentially can cause disease.

Warnings

For external use only. Flammable. Keep away from heat or flame

Do not use

- in children less than 2 months of age
- on open skin wounds

When using this product keep out of eyes, ears, and mouth. In case of contact with eyes, rinse eyes thoroughly with water.
Stop use and ask a doctor if irritation or rash occurs. These may be signs of a serious condition.
Keep out of reach of children. If swallowed, get medical help or contact a Poison Control Center right away.

Stop use and ask a doctor if irritation or rash occurs.

Keep out of reach of children. If swallowed, get medical help or contact a Poison Control Center right away.

Directions

- Place enough product on hands to cover all surfaces. Rub hands together until dry.
- Children under 6 years of age should be supervised when using this product.

Other information

- Store between 15-30C (59-86F)
- Avoid freezing and excessive heat above 40C (104F)

Inactive ingredients

Glycerin, Propylene Glycol, Monoethanolamine, purified water USP

RECENT MAJOR CHANGES

Label Update